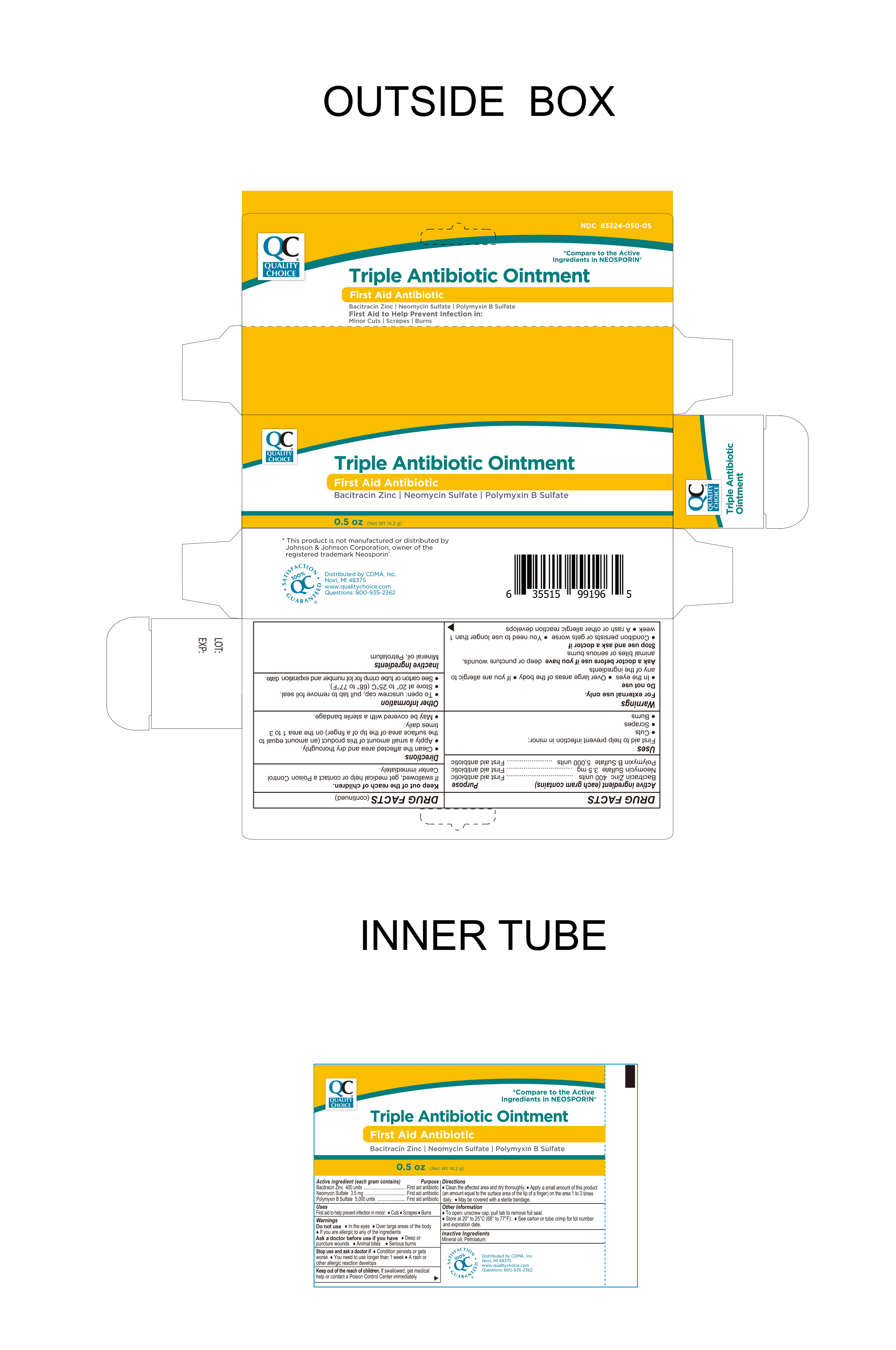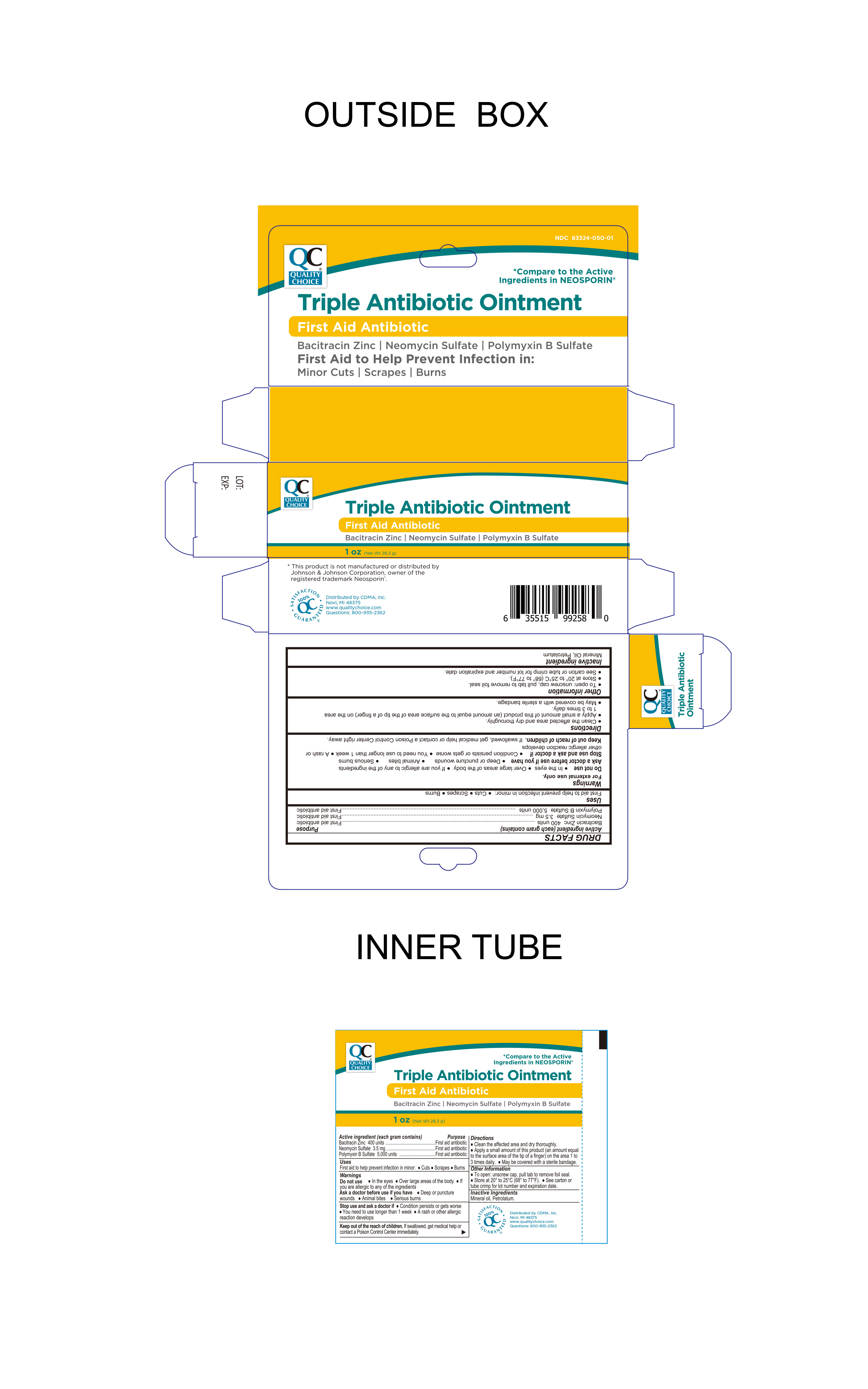 DRUG LABEL: QC Triple Antibiotic
NDC: 83324-050 | Form: OINTMENT
Manufacturer: Chain Drug Marketing Association
Category: otc | Type: HUMAN OTC DRUG LABEL
Date: 20240604

ACTIVE INGREDIENTS: BACITRACIN ZINC 400 [USP'U]/1 g; NEOMYCIN SULFATE 3.5 mg/1 g; POLYMYXIN B SULFATE 5000 [USP'U]/1 g
INACTIVE INGREDIENTS: MINERAL OIL; PETROLATUM

Quality Choice Triple Antibiotic Ointment
First Aid Antibiotic

Active ingredients (each gram contains)

Bacitracin zinc 400 units
Neomycin sulfate 3.5 mg
Polymyxin B sulfate 5,000 units

Purpose

First Aid Antibiotic Ointment

INDICATIONS AND USAGE

Uses first aid to help prevent infection in minor:● cuts ● scrapes ● burns

Warnings

For external use only.

Do not use

- In the eyes
- Over large areas of the body
- If you are allergic to any of the ingredients

Stop Use and ask a doctor if

- Condition persists or gets worse
- You need to use longer than 1 week
- A rash or other allergic reaction develops

Ask Doctor before use if you have

- Deep or puncture wounds
- Animal bites
- Serious burns

Keep out of reach of children.If swallowed, get medical help or contact a Poison Control Center immediately.

Directions

● clean the affected area and dry thoroughly.

● apply a small amount of this product (an amount equal to the surface area of the tip of a finger) on the area 1 to 3 times daily

● may be covered with a sterile bandage.

Other information

● To open: unscrew cap, pull tab to remove foil seal
● store at 20° to 25°C (68° to 77°F)

● see carton or tube crimp for lot number and expiration date.

Inactive ingredientMineral Oil, Petrolatum

Distributed by CDMA., Inc. ©
43157 W 9 Mile Rd.

Novi, MI. 48375

www.qualitychoice.com

Questions: 800-935-2362

Other Information:

This product is not manufactured or distributed by

Johnson & Johnson Corporation, owner of the registered trademark Neosporin®